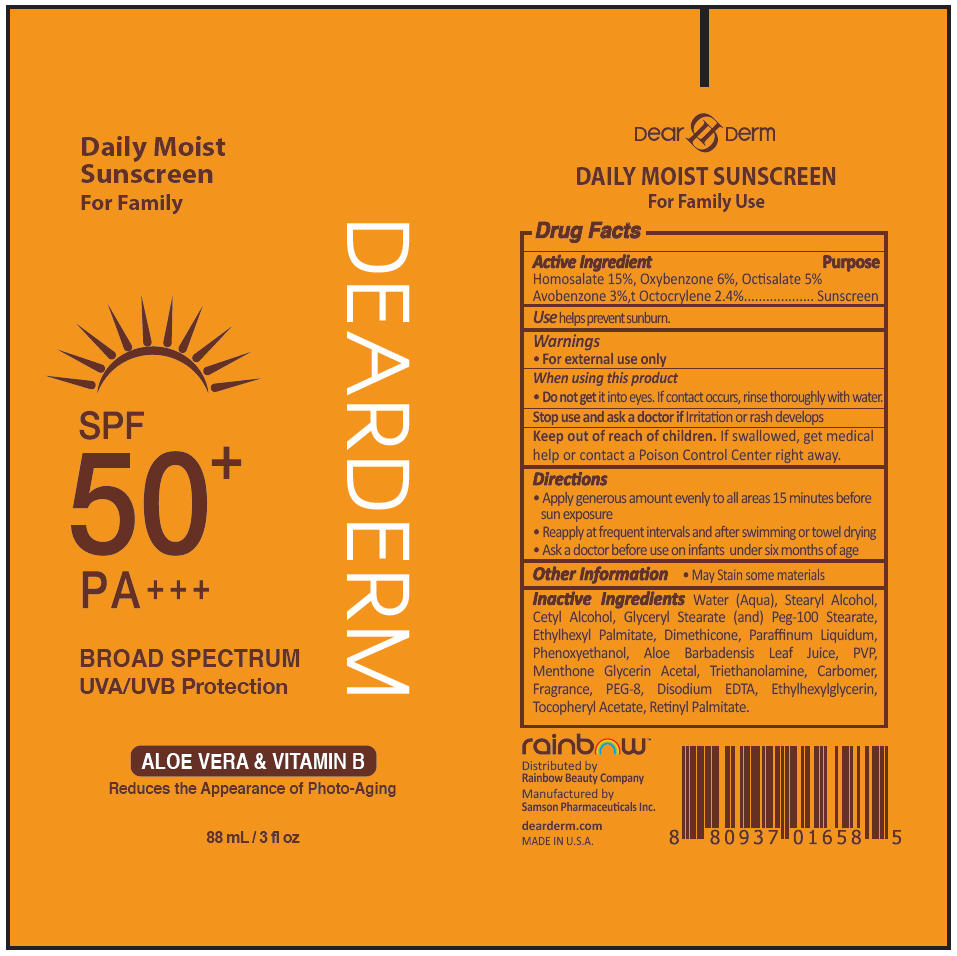 DRUG LABEL: DEARDERM DAILY MOSITURE SUNSCREEN
NDC: 72279-078 | Form: LOTION
Manufacturer: RAINBOW BEAUTY COMPANY
Category: otc | Type: HUMAN OTC DRUG LABEL
Date: 20200121

ACTIVE INGREDIENTS: Avobenzone 30 mg/1 mL; Homosalate 150 mg/1 mL; Octisalate 50 mg/1 mL; Octocrylene 24 mg/1 mL; Oxybenzone 60 mg/1 mL
INACTIVE INGREDIENTS: Water; Stearyl Alcohol; Cetyl Alcohol; Glyceryl Monostearate; PEG-100 Stearate

DEARDERM DAILY MOISTURE SUNSCREEN

Drug Facts

Active Ingredient

Homosalate 15%, Oxybenzone 6%, Octisalate 5% Avobenzone 3%,t Octocrylene 2.4%

Purpose

Sunscreen

Use

helps prevent sunburn.

Warnings

- For external use only

When using this product

- Do not get it into eyes. If contact occurs, rinse thoroughly with water.

Stop use and ask a doctor if Irritation or rash develops

Keep out of reach of children. If swallowed, get medical help or contact a Poison Control Center right away.

Directions

- Apply generous amount evenly to all areas 15 minutes before sun exposure
- Reapply at frequent intervals and after swimming or towel drying
- Ask a doctor before use on infants under six months of age

Other Information

- May Stain some materials

Inactive Ingredients

Water (Aqua), Stearyl Alcohol, Cetyl Alcohol, Glyceryl Stearate (and) Peg-100 Stearate, Ethylhexyl Palmitate, Dimethicone, Paraffinum Liquidum, Phenoxyethanol, Aloe Barbadensis Leaf Juice, PVP, Menthone Glycerin Acetal, Triethanolamine, Carbomer, Fragrance, PEG-8, Disodium EDTA, Ethylhexylglycerin, Tocopheryl Acetate, Retinyl Palmitate.

Distributed by
Rainbow Beauty Company

Manufactured by
Samson Pharmaceuticals Inc.

PRINCIPAL DISPLAY PANEL - 88 mL Tube Label

Daily Moist
Sunscreen
For Family

DEARDERM

SPF
50^+
PA+++

BROAD SPECTRUM
UVA/UVB Protection

ALOE VERA & VITAMIN B

Reduces the Appearance of Photo-Aging

88 mL / 3 fl oz